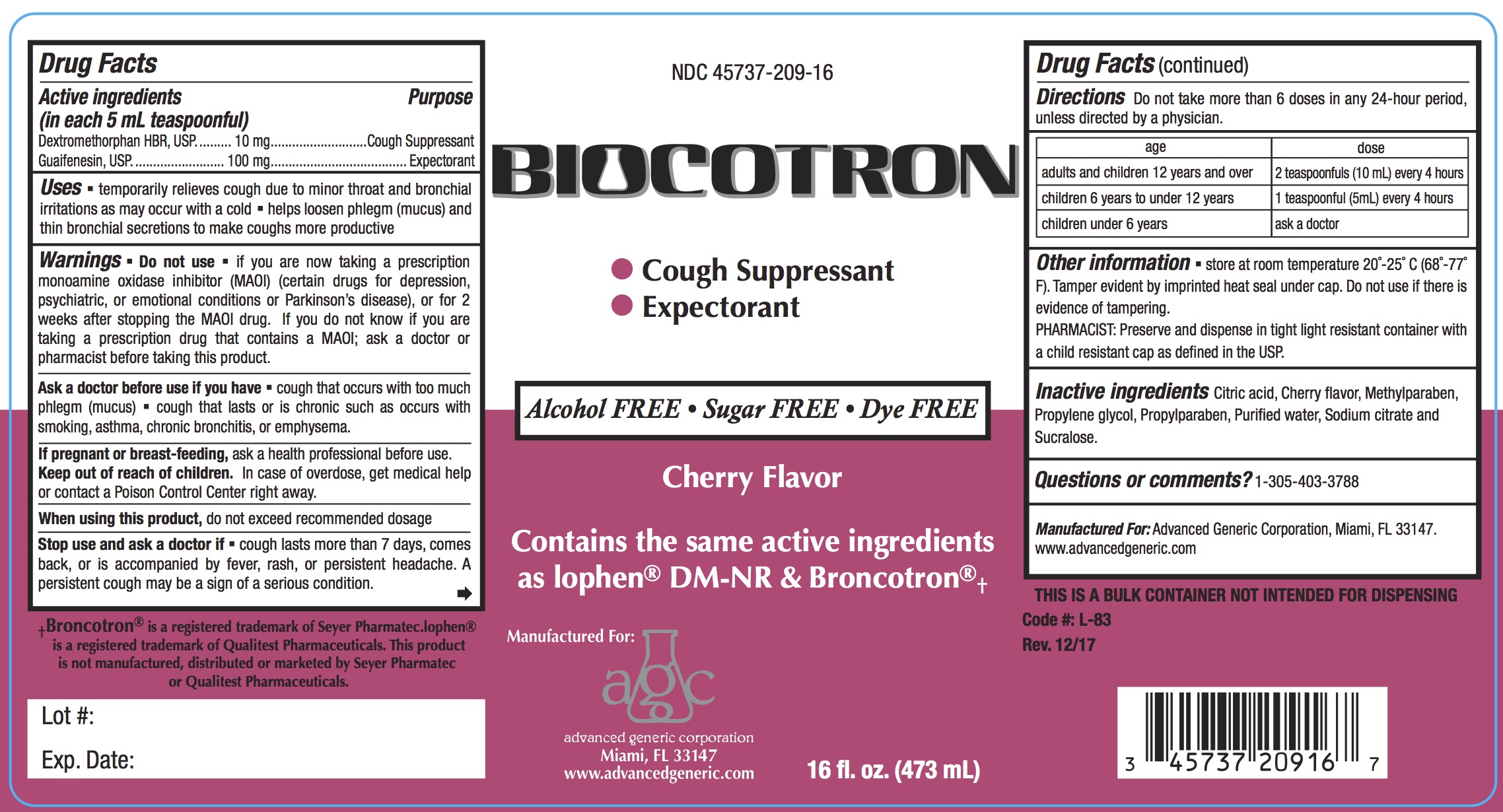 DRUG LABEL: Biocotron
NDC: 45737-209 | Form: LIQUID
Manufacturer: Advanced Generic Corporation
Category: otc | Type: HUMAN OTC DRUG LABEL
Date: 20241226

ACTIVE INGREDIENTS: DEXTROMETHORPHAN HYDROBROMIDE 10 mg/5 mL; GUAIFENESIN 100 mg/5 mL
INACTIVE INGREDIENTS: CITRIC ACID MONOHYDRATE; WATER; METHYLPARABEN; PROPYLENE GLYCOL; SODIUM CITRATE; PROPYLPARABEN; SUCRALOSE

AGC-Biocotron 209

Active Ingredients: (in each 5 mL tsp.) Purpose
Dextromethorphan Hydrobromide 10 mg.................. Cough Suppressant
Guaifenesin 100 mg .............................................. Expectorant

Purpose

Cough suppressant

Expectorant

Ask a doctor before use if you have

- cough that occurs with too much phlegm (mucus)
- cough that lasts or is chronic such as occurs with smoking, asthma, chronic bronchitis, or emphysema.

When using this product,

do not exceed recommended dosage

Stop use and ask a doctor ifcough lasts more than 7 days, comes back, or is accompanied by fever, rash, or persistent headache. A persistent cough may be a sign of a serious condition.

Do not Use

If you are now taking a prescription monoamine oxidase inhibitor (MAOI) (certain drugs for depression, psychiatric or emotional conditions or Parkinson’s disease), or for 2 weeks after stopping the MAOI drug. If you do not know if you are taking a prescription drug that contains an MAOI;ask your doctor or pharmacist before taking this product.

PREGNANCY OR BREAST FEEDING

If pregnant or breast-feeding,ask a health professional before use.

Keep out of reach of children. In case of overdose, get medical help or contact a Poison Control Center right away.

DOSAGE AND ADMINISTRATION

Directions Do not take more than 6 doses in any 24-hour period, unless directed by a physician.

Age | Dose
adults and children 12 years and over | 2 teaspoonfuls (10 mL) every 4 hours
children 6 years to under 12 years | 1 teaspoonful (5 mL) every 4 hours
children under 6 years | ask a doctor

Uses

- temporarily relieves cough due to minor throat and bronchial irritations as may occur with a cold
- helps loosen phlegm (mucus) and thin bronchial secretions to make coughs more productive

INACTIVE INGREDIENT

Inactive ingredients citric acid, cherry flavor, methylparaben, propylene glycol, propylparaben, purified water, sodium citrate and sucralose

Questions or comments?1-305-403-3788
Manufactured For:Advanced Generic Corporation, Miami, FL 33166.
www.advancedgeneric.com